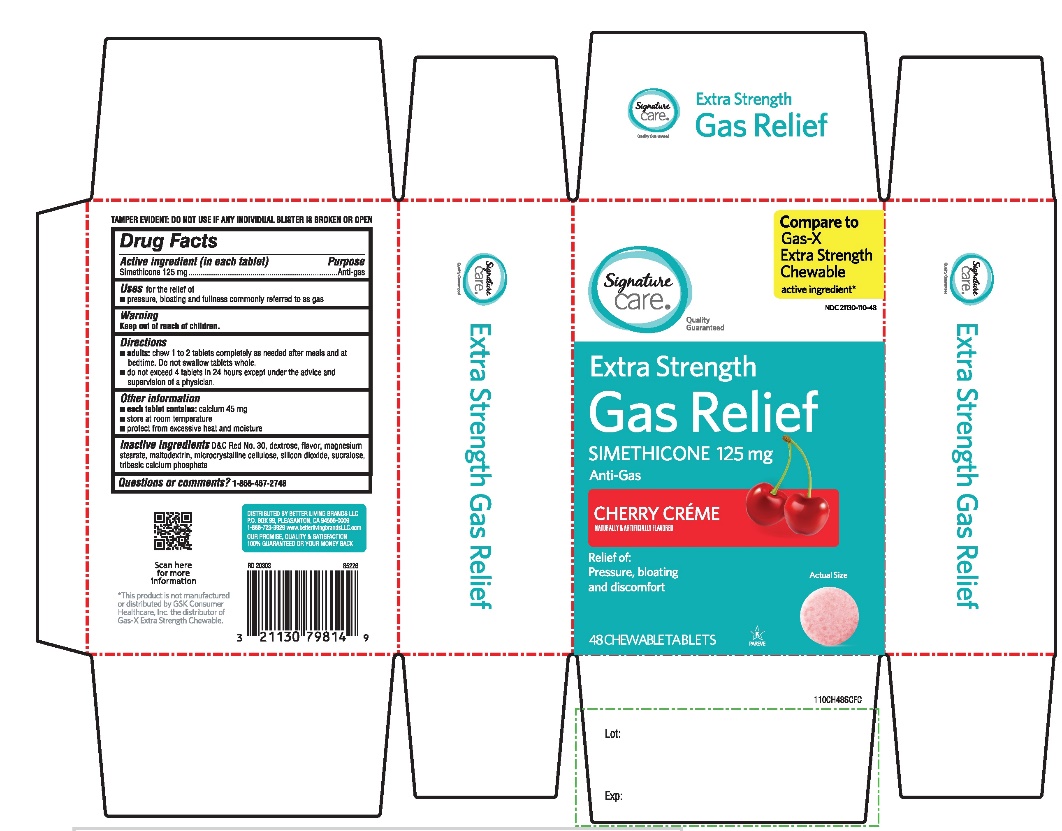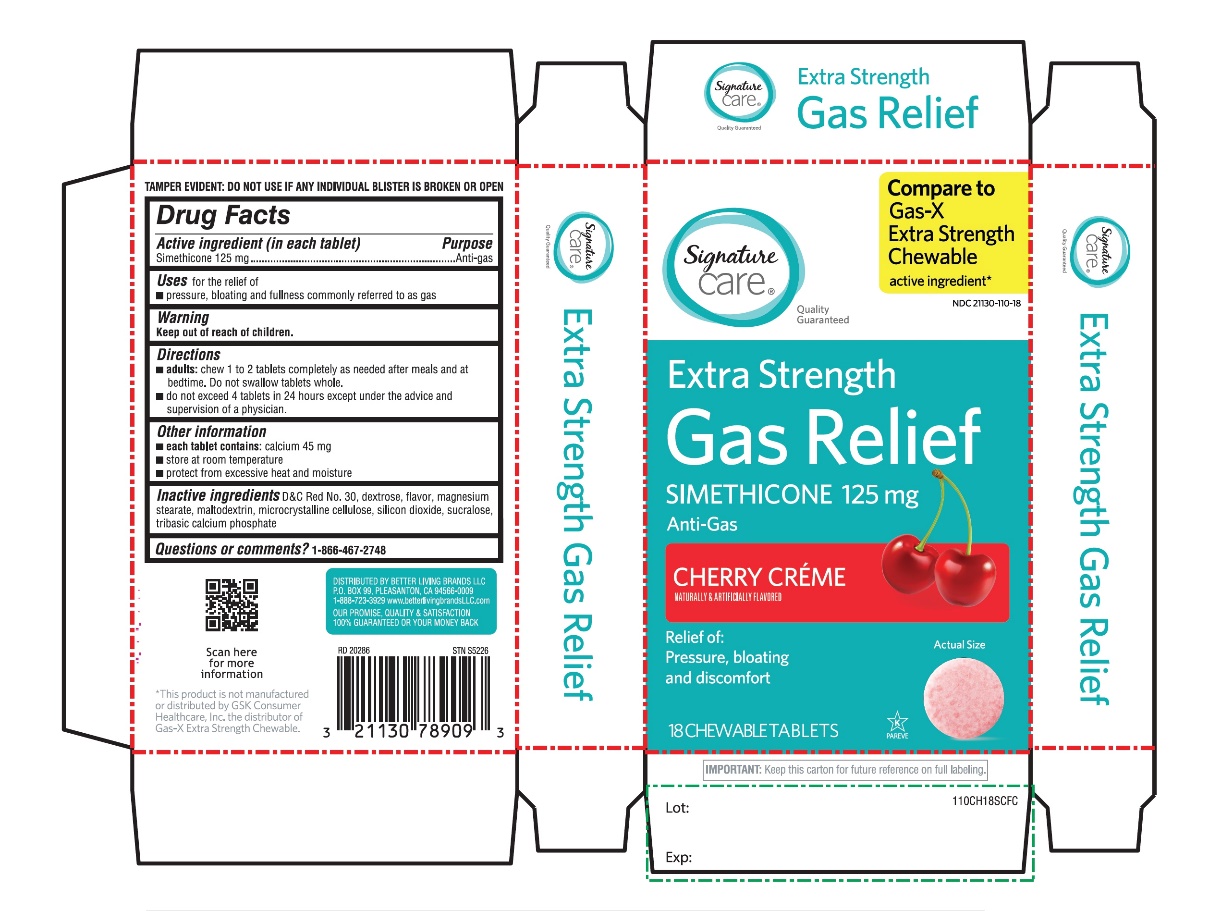 DRUG LABEL: Extra Strength Gas Relief
NDC: 21130-110 | Form: TABLET, CHEWABLE
Manufacturer: SAFEWAY
Category: otc | Type: HUMAN OTC DRUG LABEL
Date: 20251029

ACTIVE INGREDIENTS: DIMETHICONE, UNSPECIFIED 125 mg/1 1
INACTIVE INGREDIENTS: D&C RED NO. 30; DEXTROSE, UNSPECIFIED FORM; MAGNESIUM STEARATE; MALTODEXTRIN; MICROCRYSTALLINE CELLULOSE; SILICON DIOXIDE; SUCRALOSE; TRIBASIC CALCIUM PHOSPHATE

Extra Strength gas relief Simethicone 125mg Cherry Crème Flavor 18 Chewable Tablets

Active ingredient (in each tablet)

Simethicone 125 mg

Purpose

Anti-gas

Uses for relief of

- pressure, bloating and fullness commonly referred to as gas.

Directions

- adults:chew 1 to 2 tablets as needed after meals and at bedtime
- do not exceed 4 tablets in 24 hours except under the advice and supervision of a physician.

Other information

- each tablet contains:calcium 45
- store at room temperature
- protect from excessive heat and moisture

Inactive ingredients

D&C Red No. 30, dextrose, flavor, magnesium stearate, maltodextrin, microcrystalline cellulose, silicon dioxide, sucralose, tribasic calcium phosphate

Questions or comments?

1-866-467-2748

Principal Display Panel

- *Compare to the active ingredient in Gas-X®Extra Strength

Extra Strength

Gas Relief

Simethicone /Antigas

For Fast Relief of Pressure, Bloating & Discomfort

Cherry Creme Flavor

Natural and Artificially Flavored

18 CHEWABLE TABLETS

DO NOT USE IF ANY INDIVIDUAL BLISTER IS BROKEN OR OPEN

*This product is not manufactured or distributed by GSK Consumer Healthcare Inc., the distributor of GAS-X®Extra Strength.

Distributed by:

IMPORTANT:Keep this carton for future reference on full labeling.

Package Label for 18 Chewable Tablets